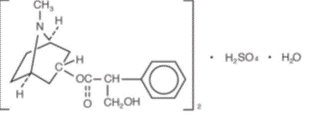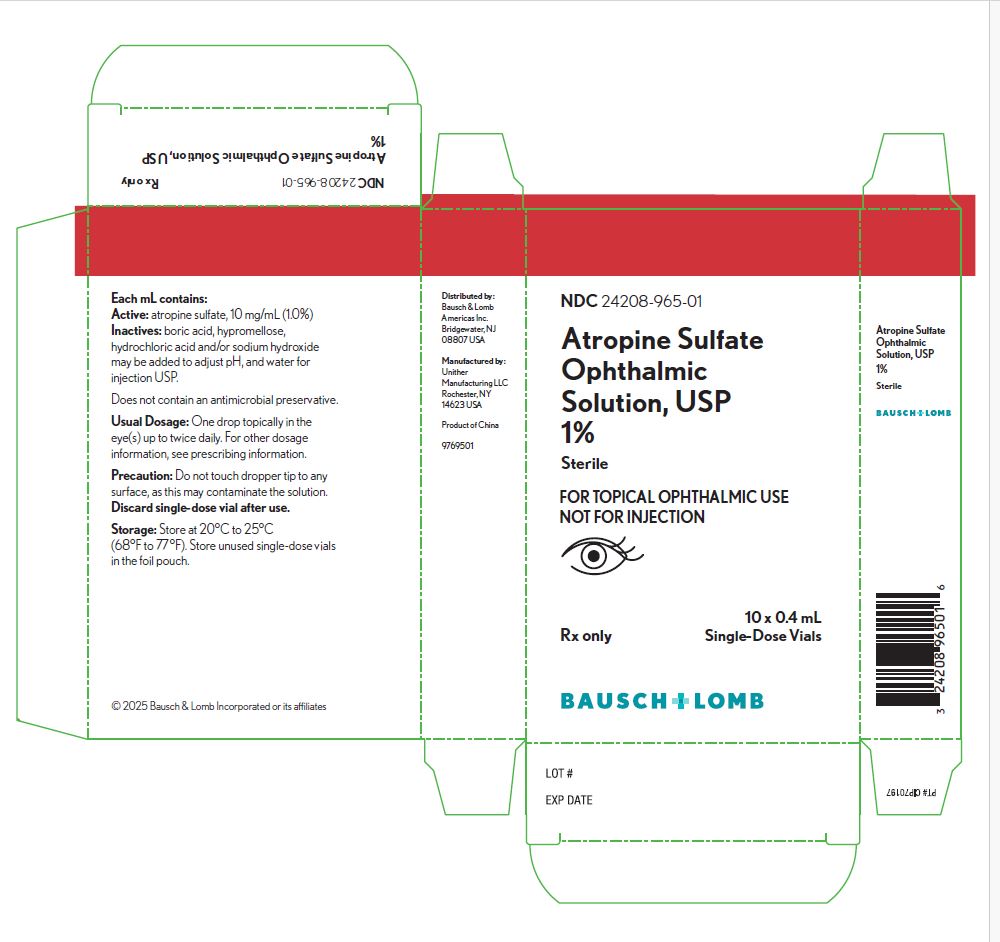 DRUG LABEL: Atropine Sulfate
NDC: 24208-965 | Form: SOLUTION
Manufacturer: Bausch & Lomb Incorporated
Category: prescription | Type: HUMAN PRESCRIPTION DRUG LABEL
Date: 20250414

ACTIVE INGREDIENTS: ATROPINE SULFATE 10 mg/1 mL
INACTIVE INGREDIENTS: BORIC ACID; HYDROCHLORIC ACID; SODIUM HYDROXIDE; WATER; HYPROMELLOSE, UNSPECIFIED

HIGHLIGHTS OF PRESCRIBING INFORMATION

These highlights do not include all the information needed to use ATROPINE SULFATE OPHTHALMIC SOLUTION, USP 1% safely and effectively. See full prescribing information for ATROPINE SULFATE OPHTHALMIC SOLUTION, USP 1%.
ATROPINE SULFATE OPHTHALMIC SOLUTION, USP 1%, for topical ophthalmic use
Initial U.S. Approval: 1960

1 INDICATIONS AND USAGE

Atropine is an anti-muscarinic agent indicated for:

- Mydriasis (1.1)
- Cycloplegia (1.2)
- Penalization of the healthy eye in the treatment of amblyopia (1.3)

2 DOSAGE AND ADMINISTRATION

- In individuals from three (3) months of age or greater, 1 drop topically to the cul-de-sac of the conjunctiva, forty minutes prior to the intended maximal dilation time (2.1).
- In individuals 3 years of age or greater, doses may be repeated up to twice daily as needed (2.2).

3 DOSAGE FORMS AND STRENGTHS

Ophthalmic solution: 1% atropine sulfate (10 mg/mL) (3).

4 CONTRAINDICATIONS

Hypersensitivity or allergic reaction to any ingredient in the formulation (4).

5 WARNINGS AND PRECAUTIONS

- Photophobia and blurred vision due to pupil unresponsiveness and cycloplegia may last up to 2 weeks (5.1).
- Risk of blood pressure increase from systemic absorption (5.2).
- To avoid the potential for eye injury or contamination, care should be taken to avoid touching the single-dose vial to the eye or to any other surface (5.3).

6 ADVERSE REACTIONS

Most common adverse reactions that have been reported are eye pain and stinging on administration, blurred vision, photophobia, superficial keratitis, decreased lacrimation, drowsiness, increased heart rate and blood pressure (6).

To report SUSPECTED ADVERSE REACTIONS, contact Bausch & Lomb Incorporated at 1-800-553-5340 or FDA at 1-800-FDA-1088 or www.fda.gov/medwatch.

7 DRUG INTERACTIONS

The use of atropine and monoamine oxidase inhibitors (MAOI) is generally not recommended because of the potential to precipitate hypertensive crisis (7).

FULL PRESCRIBING INFORMATION

1 INDICATIONS AND USAGE

Atropine Sulfate Ophthalmic Solution, USP 1% is indicated for:

2 DOSAGE AND ADMINISTRATION

In individuals from three (3) months of age or greater, 1 drop topically to the cul-de-sac of the conjunctiva in one or both eyes as indicated, forty minutes prior to the intended maximal dilation time.

In individuals 3 years of age or greater, doses may be repeated up to twice daily as needed.

Discard the single-dose vial immediately after use in one or both eyes.

3 DOSAGE FORMS AND STRENGTHS

Atropine Sulfate Ophthalmic Solution, USP 1%: each mL contains 10 mg of atropine sulfate.

4 CONTRAINDICATIONS

Atropine Sulfate Ophthalmic Solution, USP 1% should not be used in anyone who has demonstrated a previous hypersensitivity or known allergic reaction to any ingredient of the formulation because it may recur.

5 WARNINGS AND PRECAUTIONS

5.1 Photophobia and Blurred Vision

Photophobia and blurred vision due to pupil unresponsiveness and cycloplegia may last up to 2 weeks.

5.2 Elevation of Blood Pressure

Elevation in blood pressure from systemic absorption has been reported following conjunctival instillation of recommended doses of Atropine Sulfate Ophthalmic Solution, USP 1%.

5.3 Potential for Eye Injury or Contamination

To avoid the potential for eye injury or contamination, care should be taken to avoid touching the single-dose vial to the eye or to any other surface.

6 ADVERSE REACTIONS

The following serious adverse reactions are described below and elsewhere in the labeling:

- Photophobia and Blurred Vision [see Warnings and Precautions (5.1)]
- Elevation in Blood Pressure [see Warnings and Precautions (5.2)]

The following adverse reactions have been identified following use of atropine sulfate ophthalmic solution. Because these reactions are reported voluntarily from a population of uncertain size, it is not always possible to reliably estimate their frequency or establish a causal relationship to drug exposure.

6.1 Ocular Adverse Reactions

Eye pain and stinging occurs upon instillation of atropine sulfate ophthalmic solution. Other commonly occurring adverse reactions include blurred vision, photophobia, superficial keratitis and decreased lacrimation. Allergic reactions such as papillary conjunctivitis, contact dermatitis, and eyelid edema may also occur less commonly.

6.2 Systemic Adverse Reactions

Systemic effects of atropine are related to its anti-muscarinic activity. Systemic adverse events reported include dryness of skin, mouth, and throat from decreased secretions from mucous membranes; drowsiness, restlessness, irritability or delirium from stimulation of the central nervous system; tachycardia; flushed skin of the face and neck.

7 DRUG INTERACTIONS

7.1 Monoamine Oxidase Inhibitors (MAOI)

The use of atropine and monoamine oxidase inhibitors (MAOI) is generally not recommended because of the potential to precipitate hypertensive crisis.

8 USE IN SPECIFIC POPULATIONS

8.1 Pregnancy

Risk Summary

There are no adequate and well-controlled studies of Atropine Sulfate Ophthalmic Solution, USP 1% administration in pregnant women to inform a drug-associated risk. Adequate animal development and reproduction studies have not been conducted with atropine sulfate. In humans, 1% atropine sulfate is systemically bioavailable following topical ocular administration [see Clinical Pharmacology (12.3)] . Atropine Sulfate Ophthalmic Solution, USP 1% should only be used during pregnancy if the potential benefit justifies the potential risk to the fetus.

8.2 Lactation

Risk Summary

There is no information to inform risk regarding the presence of atropine in human milk following ocular administrations of Atropine Sulfate Ophthalmic Solution, USP 1% to the mother. The effects on breastfed infants and the effects on milk production are also unknown. The developmental and health benefits of breastfeeding should be considered along with the mother’s clinical need for Atropine Sulfate Ophthalmic Solution, USP 1% and any potential adverse effects on the breastfed child from Atropine Sulfate Ophthalmic Solution, USP 1%.

8.4 Pediatric Use

Due to the potential for systemic absorption, the use of Atropine Sulfate Ophthalmic Solution, USP 1% in children under the age of 3 months is not recommended and the use in children under 3 years of age should be limited to no more than one drop per eye per day. Safety and efficacy in children above the age of 3 months has been established in adequate and well controlled trials.

8.5 Geriatric Use

No overall differences in safety and effectiveness have been observed between elderly and younger adult patients.

10 OVERDOSAGE

In the event of accidental ingestion or toxic overdosage with Atropine Sulfate Ophthalmic Solution, USP 1%, supportive care may include a short acting barbiturate or diazepam as needed to control marked excitement and convulsions. Large doses for sedation should be avoided because central depressant action may coincide with the depression occurring late in atropine poisoning. Central stimulants are not recommended.

Physostigmine, given by slow intravenous injection of 1 to 4 mg (0.5 to 1 mg in pediatric populations), rapidly abolishes delirium and coma caused by large doses of atropine. Since physostigmine is rapidly destroyed, the patient may again lapse into coma after one to two hours, and repeated doses may be required.

Artificial respiration with oxygen may be necessary. Cooling measures may be needed to help to reduce fever, especially in pediatric populations.

The fatal adult dose of atropine is not known. In pediatric populations, 10 mg or less may be fatal.

11 DESCRIPTION

Atropine Sulfate Ophthalmic Solution, USP 1% is an aseptically prepared, sterile solution for topical ophthalmic use. The product does not contain an antimicrobial preservative. The active ingredient is represented by the chemical structure:

Chemical Name: Benzeneacetic acid, α-(hydroxymethyl)-, 8-methyl-8-azabicyclo[3.2.1.]oct-3-yl ester, endo –(±)-, sulfate (2:1) (salt), monohydrate.

Molecular Formula: (C17H23NO3)2• H2SO4• H2O

Molecular Weight: 694.84 g/mol

Each mL of Atropine Sulfate Ophthalmic Solution, USP 1% contains: Active:atropine sulfate 10 mg equivalent to 8.3 mg of atropine.

Inactives:boric acid, hydroxypropyl methylcellulose, hydrochloric acid and/or sodium hydroxide may be added to adjust pH (3.5 to 6.0), and water for injection USP.

12 CLINICAL PHARMACOLOGY

12.1 Mechanism of Action

Atropine is a reversible antagonist of muscarine-like actions of acetylcholine and is therefore classified as an anti-muscarinic agent. Atropine is relatively selective for muscarinic receptors. Its potency at nicotinic receptors is much lower, and actions at non-muscarinic receptors are generally undetectable clinically. Atropine does not distinguish among the M1, M2, and M3 subgroups of muscarinic receptors.

The pupillary constrictor muscle depends on muscarinic cholinoceptor activation. This activation is blocked by topical atropine resulting in unopposed sympathetic dilator activity and mydriasis. Atropine also weakens the contraction of the ciliary muscle, or cycloplegia. Cycloplegia results in loss of the ability to accommodate such that the eye cannot focus for near vision.

12.2 Pharmacodynamics

The onset of action after administration of Atropine Sulfate Ophthalmic Solution, USP 1% generally occurs within minutes with maximal effect seen in hours and the effect can last multiple days [see Clinical Studies (14)] .

12.3 Pharmacokinetics

In a study of healthy subjects, after topical ocular administration of 30 μL of atropine sulfate ophthalmic solution 1%, the mean (± SD) systemic bioavailability of l-hyoscyamine was reported to be approximately 64 ± 29% (range 19% to 95%) as compared to intravenous administration of atropine sulfate. The median (range) time to maximum plasma concentration (Tmax) was 19 minutes (range 3 to 60 minutes), and the mean (±SD) peak plasma concentration (Cmax) of l-hyoscyamine was 288 ± 73 pg/mL. The mean (±SD) plasma half-life was reported to be approximately 2.5 ± 0.8 hours.

In a separate study of patients undergoing ocular surgery, after topical ocular administration of 40 μL of atropine sulfate ophthalmic solution, 1%, the mean (± SD) plasma Cmax of l-hyoscyamine was 860 ± 402 pg/mL, which was observed within 8 minutes following administration.

13 NONCLINICAL TOXICOLOGY

13.1 Carcinogenesis, Mutagenesis, Impairment of Fertility

Atropine sulfate was negative in the Salmonella/microsome mutagenicity test. Studies to evaluate carcinogenicity and impairment of fertility have not been conducted.

14 CLINICAL STUDIES

Topical administration of Atropine Sulfate Ophthalmic Solution, USP 1% results in mydriasis and/or cycloplegia with efficacy demonstrated in both adults and children. The maximum effect for mydriasis is achieved in about 30–40 minutes after administration, with recovery after approximately 7–10 days. The maximum effect for cycloplegia is achieved within 60–180 minutes after administration, with recovery after approximately 7–12 days.

16 HOW SUPPLIED/STORAGE AND HANDLING

Atropine Sulfate Ophthalmic Solution, USP 1% is supplied as an aseptically prepared, sterile solution for topical ophthalmic use supplied as a 0.4 mL fill in a translucent, low-density polyethylene, single-dose vial. One (1) strip of 5 single-dose vials is packaged into a foil pouch.

- NDC 24208-965-01 10 single-dose vials. 2 foil pouches each containing one strip of 5 single-dose vials.

Storage and Handling:

Store at 20°C to 25°C (68°F to 77°F).

Store single-dose vials in the foil pouches. Opened vials cannot be resealed and should be discarded immediately after use.

17 PATIENT COUNSELING INFORMATION

- Advise patients that drops will sting upon instillation that they may experience blurry vision and sensitivity to light and should protect their eyes in bright illumination during dilation. These effects may last up to a couple weeks.
- Advise patients to keep the single-dose vials in the foil pouches until ready to use. The solution from one single-dose vial is to be used immediately after opening to dose one or both eye(s) of a single patient. The single-dose vial, including any remaining contents, should be discarded immediately after administration [see Dosage and Administration (2)] .
- Advise patients not to touch the tip of the single-dose vial to their eye or to any surface, in order to avoid eye injury or contamination of the solution.

Distributed by:
Bausch & Lomb Americas Inc.
Bridgewater, NJ 08807 USA

© 2022 Bausch & Lomb Incorporated or its affiliates

9775700

Package/Label Display Panel

NDC24208-965-01

Atropine Sulfate
Ophthalmic
Solution, USP
1%

Sterile

FOR TOPICAL OPHTHALMIC USE
NOT FOR INJECTION

EYE IMAGE

Rx only
10 x 0.4 mL
Single-Dose Vials

BAUSCH + LOMB

9769501